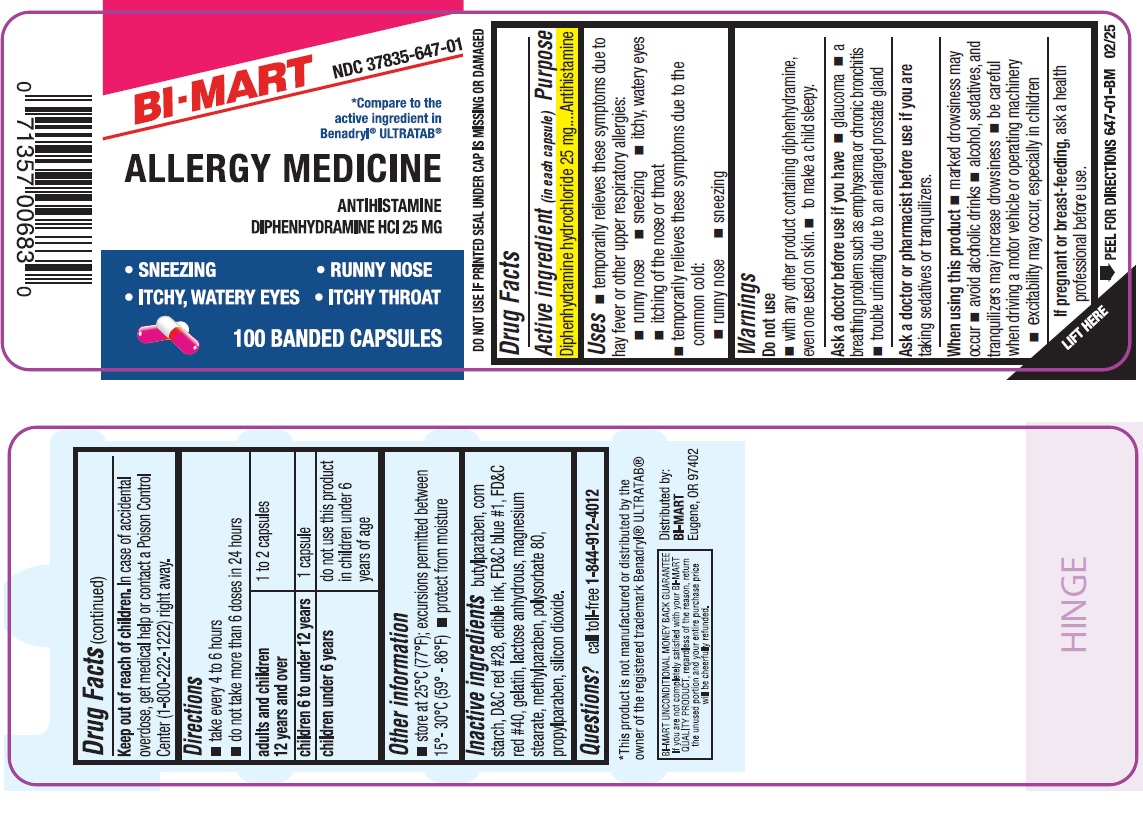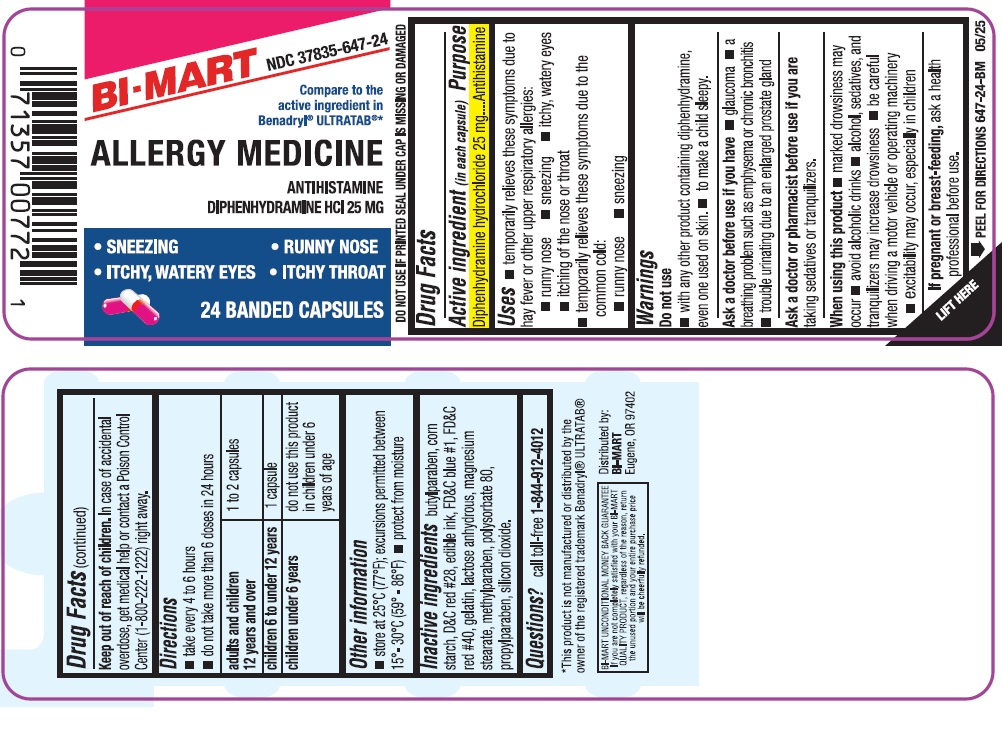 DRUG LABEL: Allergy Medicine
NDC: 37835-647 | Form: CAPSULE
Manufacturer: Bi-Mart
Category: otc | Type: HUMAN OTC DRUG LABEL
Date: 20250601

ACTIVE INGREDIENTS: DIPHENHYDRAMINE HYDROCHLORIDE 25 mg/1 1
INACTIVE INGREDIENTS: BUTYLPARABEN; STARCH, CORN; D&C RED NO. 28; FD&C BLUE NO. 1; FD&C RED NO. 40; GELATIN, UNSPECIFIED; ANHYDROUS LACTOSE; MAGNESIUM STEARATE; METHYLPARABEN; POLYSORBATE 80; PROPYLPARABEN; SILICON DIOXIDE

Active ingredient (in each capsule)

Diphenhydramine hydrochloride 25 mg

Purpose

Antihistamine

Uses

- temporarily relieves these symptoms due to hay fever or other upper respiratory allergies:
  - runny nose
  - sneezing
  - itchy, watery eyes
  - itching of the nose or throat
- temporarily relieves these symptoms due to the common cold:
  - runny nose
  - sneezing

Warnings

Do not use

- with any other product containing diphenhydramine, even one used on skin
- to make a child sleepy.

Ask a doctor before use if you have

- glaucoma
- a breathing problem such as emphysema or chronic bronchitis
- trouble urinating due to enlarged prostate gland

Ask a doctor or pharmacist before use if you are

taking sedatives or tranquilizers.

When using this product

- marked drowsiness may occur
- avoid alcoholic drinks
- alcohol, sedatives, and tranquilizers may increase drowsiness
- be careful when driving a motor vehicle or operating machinery
- excitability may occur, especially in children

If pregnant or breast-feeding,

ask a health professional before use.

Keep out of reach of children.

In case of accidental overdose, get medical help or contact a Poison Control Center (1-800-222-1222) right away.

Directions

- take every 4 to 6 hours
- do not take more than 6 doses in 24 hours

adults and children 12 years and over | 1 to 2 capsules
children 6 to under 12 years | 1 capsule
children under 6 years | do not use this product in children under 6 years of age

Other information

- store at 25°C (77°F); excursions permitted between 15°-30°C (59°-86°F)
- protect from moisture

Inactive ingredients

butylparaben, corn starch, D&C red #28, edible ink, FD&C blue #1, FD&C red #40, gelatin, lactose anhydrous, magnesium stearate, methylparaben, polysorbate 80, propylparaben, silicon dioxide.

Questions?

call toll-free 1-844-912-4012

Distributed by

BI-MART

Eugene, OR 97402